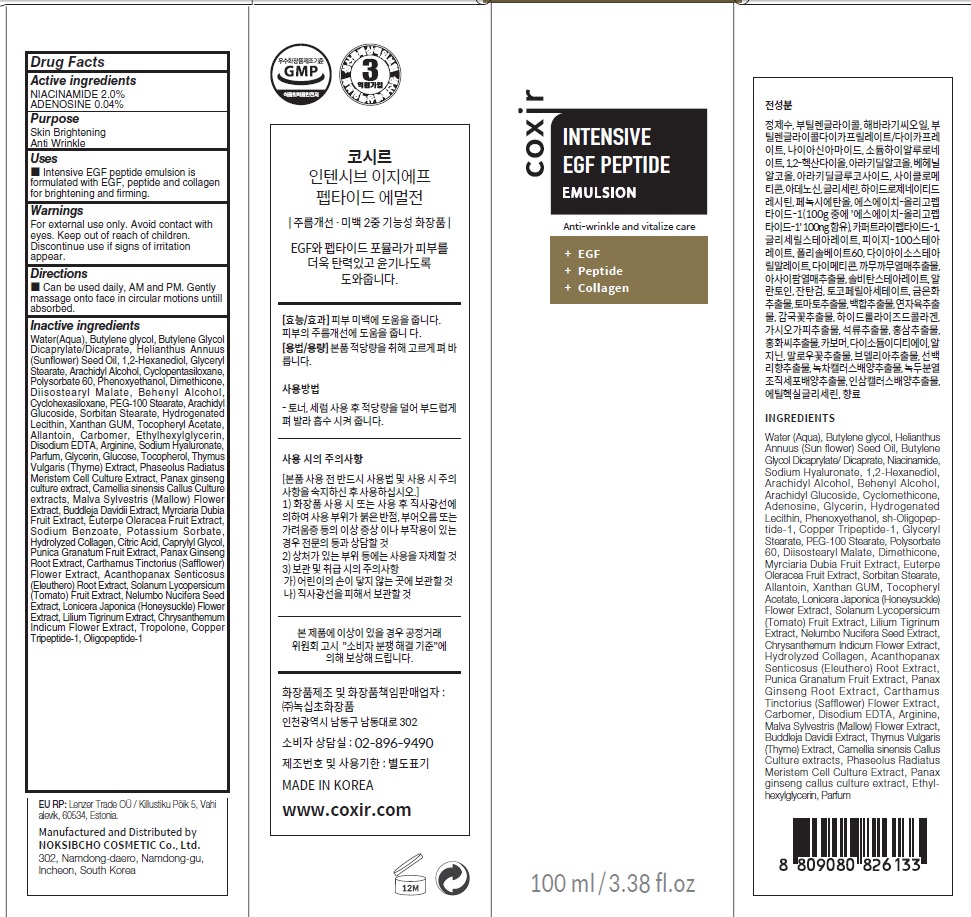 DRUG LABEL: COXIR INTENSIVE EGF PEPTIDE
NDC: 73590-0072 | Form: EMULSION
Manufacturer: NOKSIBCHO cosmetic Co., Ltd.
Category: otc | Type: HUMAN OTC DRUG LABEL
Date: 20210714

ACTIVE INGREDIENTS: NIACINAMIDE 2.0 g/100 mL; ADENOSINE 0.04 g/100 mL
INACTIVE INGREDIENTS: Water; Butylene Glycol; BUTYLENE GLYCOL DICAPRYLATE/DICAPRATE

Drug Facts

ACTIVE INGREDIENTS

NIACINAMIDE 2.0%
ADENOSINE 0.04%

INACTIVE INGREDIENTS

Water(Aqua), Butylene glycol, Butylene Glycol Dicaprylate/Dicaprate, Helianthus Annuus (Sunflower) Seed Oil, 1,2-Hexanediol, Glyceryl Stearate,
Arachidyl Alcohol, Cyclopentasiloxane, Polysorbate 60, Phenoxyethanol, Dimethicone, Diisostearyl Malate, Behenyl Alcohol, Cyclohexasiloxane, PEG-100 Stearate, Arachidyl Glucoside, Sorbitan Stearate, Hydrogenated Lecithin, Xanthan GUM, Tocopheryl Acetate, Allantoin, Carbomer, Ethylhexylglycerin, Disodium EDTA, Arginine, Sodium Hyaluronate, Parfum, Glycerin, Glucose, Tocopherol, Thymus Vulgaris (Thyme) Extract, Phaseolus Radiatus Meristem Cell Culture Extract, Panax ginseng culture extract, Camellia sinensis Callus Culture extracts, Malva Sylvestris (Mallow) Flower Extract, Buddleja Davidii Extract, Myrciaria Dubia Fruit Extract, Euterpe Oleracea Fruit Extract, Sodium Benzoate, Potassium Sorbate, Hydrolyzed Collagen, Citric Acid, Caprylyl Glycol, Punica Granatum Fruit Extract, Panax Ginseng Root Extract, Carthamus Tinctorius (Safflower) Flower Extract, Acanthopanax Senticosus (Eleuthero) Root Extract, Solanum Lycopersicum (Tomato) Fruit Extract,
Nelumbo Nucifera Seed Extract, Lonicera Japonica (Honeysuckle) Flower Extract, Lilium Tigrinum Extract, Chrysanthemum Indicum Flower Extract, Tropolone, Copper Tripeptide-1, Oligopeptide-1

PURPOSE

Skin Brightening
Anti wrinkle

WARNINGS

For external use only.
Avoid contact with eyes.
Keep out of reach of children.
Discontinue use if signs of irritation appear.

KEEP OUT OF REACH OF CHILDREN

Uses

■ Intensive EGF peptide emulsion is formulated with EGF, peptide and collagen for brightening and firming.

Directions

■ Can be used daily, AM and PM. Gently massage onto face in circular motions untill absorbed.